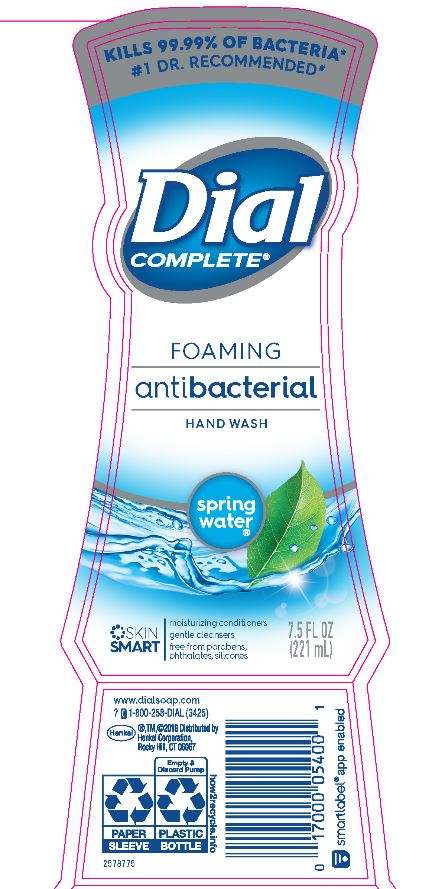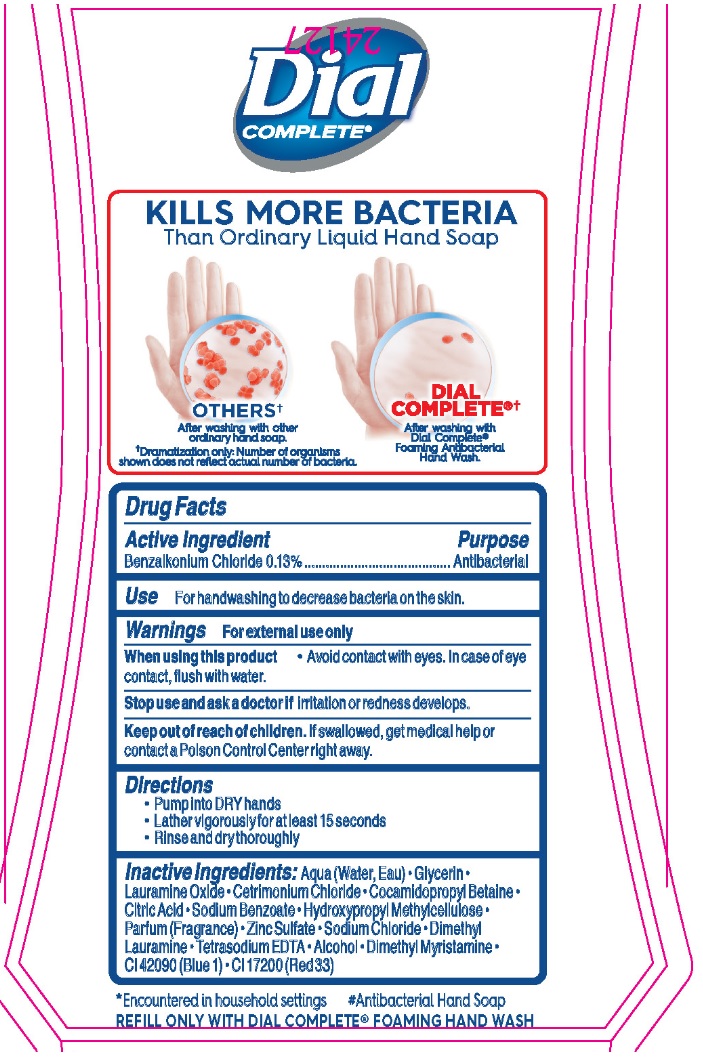 DRUG LABEL: Dial Complete Spring Water FHW
NDC: 50663-242 | Form: SOLUTION
Manufacturer: Zotos International Inc
Category: otc | Type: HUMAN OTC DRUG LABEL
Date: 20200417

ACTIVE INGREDIENTS: BENZALKONIUM CHLORIDE 0.13 g/100 mL
INACTIVE INGREDIENTS: WATER 94.27 mL/100 mL

Benzalkonium Chloride 0.13%

Active ingredient Purpose

Benzalkonium Chloride 0.13%......................................... Antibacterial

Purpose

Antibacterial

Use

For handwashing to decrease bacteria on the skin.

Warning

For external use only.

When using this product • Avoid contact with eyes. In case of eye
contact, flush with water.

Stop use and ask a doctor if irritation or redness develops.

Keep out of reach of children. If swallowed, get medical help or
contact a Poison Control Center right away.

Directions

• Pump into DRY hands
• Lather vigorously for at least 15 seconds
• Rinse and dry thoroughly

Inactive Ingredients

Inactive Ingredients: Aqua (Water, Eau) • Glycerin •
Lauramine Oxide • Cetrimonium Chloride • Cocamidopropyl Betaine •
Citric Acid • Sodium Benzoate • Hydroxypropyl Methylcellulose •
Parfum (Fragrance) • Zinc Sulfate • Sodium Chloride • Dimethyl
Lauramine • Tetrasodium EDTA • Alcohol • Dimethyl Myristamine •
CI 42090 (Blue 1) • CI 17200 (Red 33)

*Encountered in household settings
#Antibacterial Hand Soap
REFILL ONLY WITH DIAL COMPLETE® FOAMING HAND WASH

Questions

1-800-258-DIAL (3425)

®,TM,©2019 Distributed by
Henkel Corporation,
Rocky Hill, CT 06067
www.dialsoap.com

DOSAGE AND ADMINISTRATION

Topical Liquid

For handwashing to decrease bacteria on the skin.

KILLS MORE BACTERIA

Than Ordinary Liquid Hand Soap